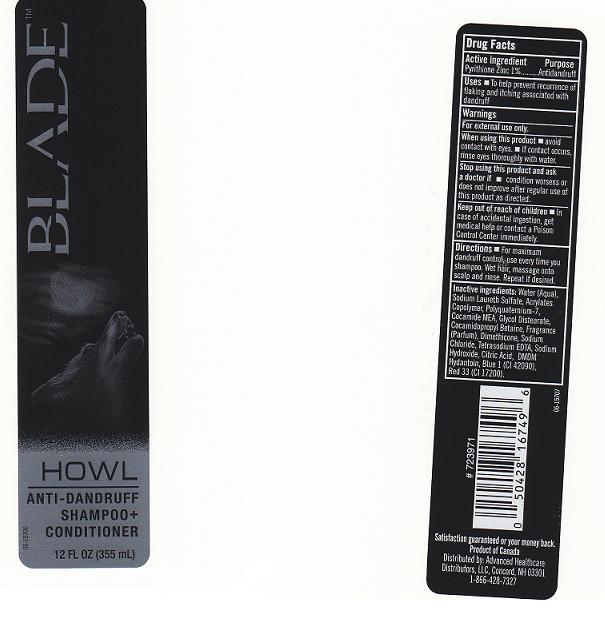 DRUG LABEL: BLADE HOWL
NDC: 59779-422 | Form: SHAMPOO
Manufacturer: CVS PHARMACY INC
Category: otc | Type: HUMAN OTC DRUG LABEL
Date: 20101103

ACTIVE INGREDIENTS: PYRITHIONE ZINC 1 mL/100 mL
INACTIVE INGREDIENTS: WATER; SODIUM LAURETH SULFATE; AMMONIO METHACRYLATE COPOLYMER TYPE A; POLYQUATERNIUM-7 (70/30 ACRYLAMIDE/DADMAC; 1600 KD); COCO MONOETHANOLAMIDE; GLYCOL DISTEARATE; COCAMIDOPROPYL BETAINE; DIMETHICONE; SODIUM CHLORIDE; EDETATE SODIUM; SODIUM HYDROXIDE; CITRIC ACID MONOHYDRATE; DMDM HYDANTOIN; FD&C BLUE NO. 1; D&C RED NO. 33

Drug Facts Box

Active Ingredient

Pyrithione Zinc 1%

Purpose

Antidandruff

Uses

To help prevent recurrence of flaking and itching associated with dandruff

Warnings

For external use only.

when using this product

Avoid contact with eyes. If contact occurs, rinse eyes thoroughly with water.

Stop using this product and ask a doctor if

condition worsens or does not improve after regular use of this product as directed.

Keep out of reach of children

In case of accidental ingestion, get medical help or contact a Poison Control Center immediately.

Directions

For maximum dandruff control, use every time you shampoo. Wet hair, massage onto scalp and rinse . Repeat if desired.

Inactive Ingredients

Water (Aqua), Sodium Laureth Sulfate, Acrylates Copolymer, Polyquaternium-7, Cocamide MEA, Glycol Distearate, Cocamidopropyl Betaine, Fragrance (Parfum), Dimethicone, Sodium Chloride, Tetrasodium EDTA, Sodium Hydroxide, Citric Acid DMDM Hydantoin, Blue 1 (CI 42090), Red 33 (CI 17200).

Package Front and Back Labels

blade.jpg